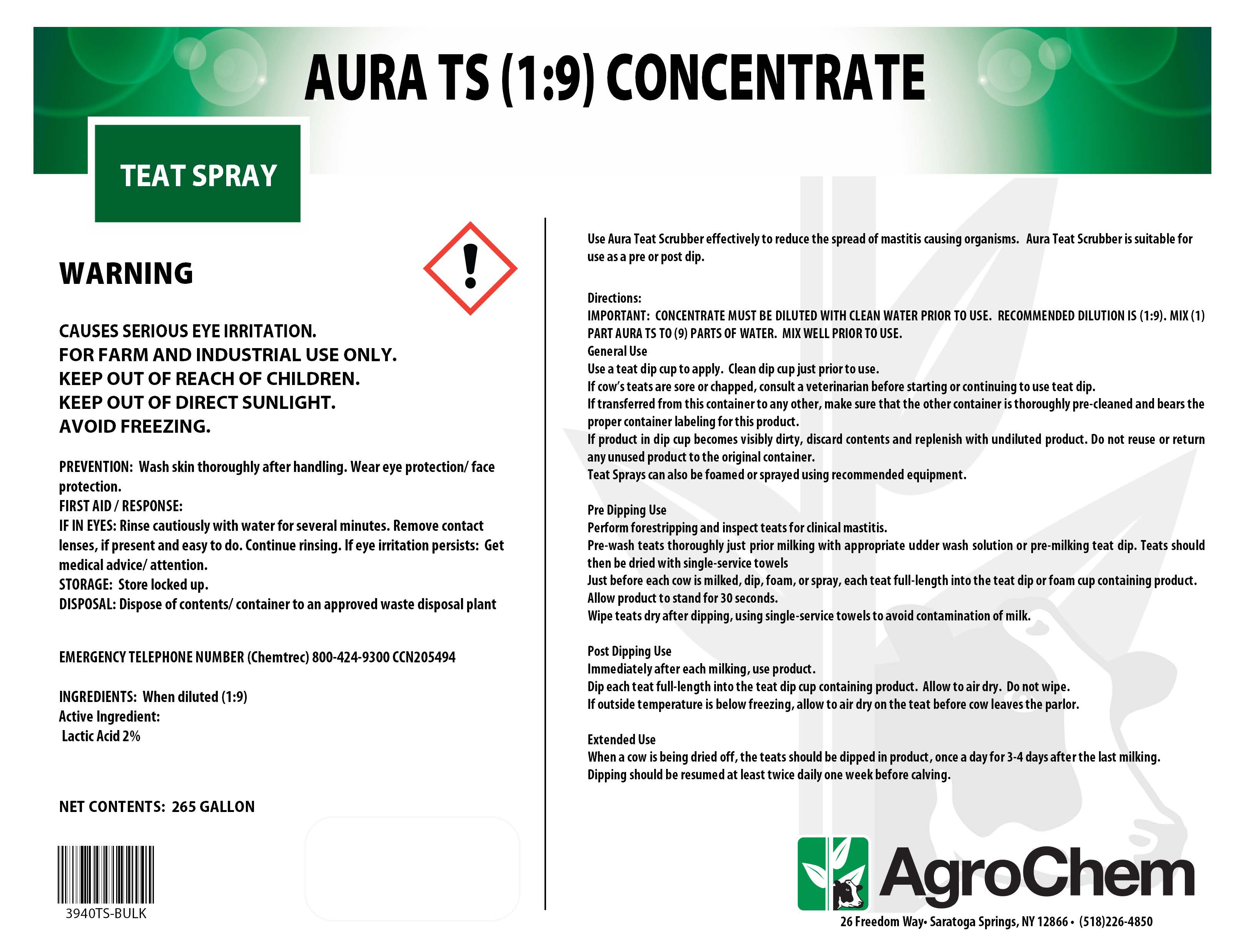 DRUG LABEL: Aura Teat Scrubber
NDC: 17307-3942 | Form: SOLUTION, CONCENTRATE
Manufacturer: AgroChem Inc
Category: animal | Type: OTC ANIMAL DRUG LABEL
Date: 20180130

ACTIVE INGREDIENTS: LACTIC ACID 0.0228 kg/1 kg
INACTIVE INGREDIENTS: SODIUM OCTYL SULFATE 0.006 kg/1 kg; CAPRYLIC/CAPRIC ACID 0.001 kg/1 kg; C10-16 PARETH-1 0.0025 kg/1 kg; C9-11 PARETH-3 0.0025 kg/1 kg; GLYCERIN 0.004 kg/1 kg; WATER 0.0612 kg/1 kg

Aura Teat Scrubber Concentrate

DESCRIPTION

AURA TS (1:9) CONCENTRATE

TEAT SPRAY

WARNING

CAUSES SERIOUS EYE IRRITATION.

FOR FARM AND INDUSTRIAL USE ONLY.

KEEP OUT OF REACH OF CHILDREN.

KEEP OUT OF DIRECT SUNLIGHT.

AVOID FREEZING.

PREVENTION: Wash skin thoroughly after handling. Wear eye protection/ face protection.

FIRST AID / RESPONSE:

IF IN EYES: Rinse cautiously with water for several minutes. Remove contact lenses, if present and easy to do. Continue rinsing. If eye irritation persists: Get medical advice/ attention.

STORAGE: Store locked up.

DISPOSAL: Dispose of contents/ container to an approved waste disposal plant

EMERGENCY TELEPHONE NUMBER (Chemtrec) 800-424-9300 CCN205494

ACTIVE INGREDIENT

INGREDIENTS: When diluted (1:9)

Active Ingredient:

Lactic Acid 2%

INSTRUCTIONS FOR USE

Use Aura Teat Scrubber effectively to reduce the spread of mastitis causing organisms. Aura Teat Scrubber is suitable for use as a pre or post dip.

Directions:

IMPORTANT: CONCENTRATE MUST BE DILUTED WITH CLEAN WATER PRIOR TO USE. RECOMMENDED DILUTION IS (1:9). MIX (1) PART AURA TS TO (9) PARTS OF WATER. MIX WELL PRIOR TO USE.

General Use

Use a teat dip cup to apply. Clean dip cup just prior to use.

If cow’s teats are sore or chapped, consult a veterinarian before starting or continuing to use teat dip.

If transferred from this container to any other, make sure that the other container is thoroughly pre-cleaned and bears the proper container labeling for this product.

If product in dip cup becomes visibly dirty, discard contents and replenish with undiluted product. Do not reuse or return any unused product to the original container.

Teat Sprays can also be foamed or sprayed using recommended equipment.

Pre Dipping Use

Perform forestripping and inspect teats for clinical mastitis.

Pre-wash teats thoroughly just prior milking with appropriate udder wash solution or pre-milking teat dip. Teats should then be dried with single-service towels

Just before each cow is milked, dip, foam, or spray, each teat full-length into the teat dip or foam cup containing product.

Allow product to stand for 30 seconds.

Wipe teats dry after dipping, using single-service towels to avoid contamination of milk.

Post Dipping Use

Immediately after each milking, use product.

Dip each teat full-length into the teat dip cup containing product. Allow to air dry. Do not wipe.

If outside temperature is below freezing, allow to air dry on the teat before cow leaves the parlor.

Extended Use

When a cow is being dried off, the teats should be dipped in product, once a day for 3-4 days after the last milking.

Dipping should be resumed at least twice daily one week before calving.